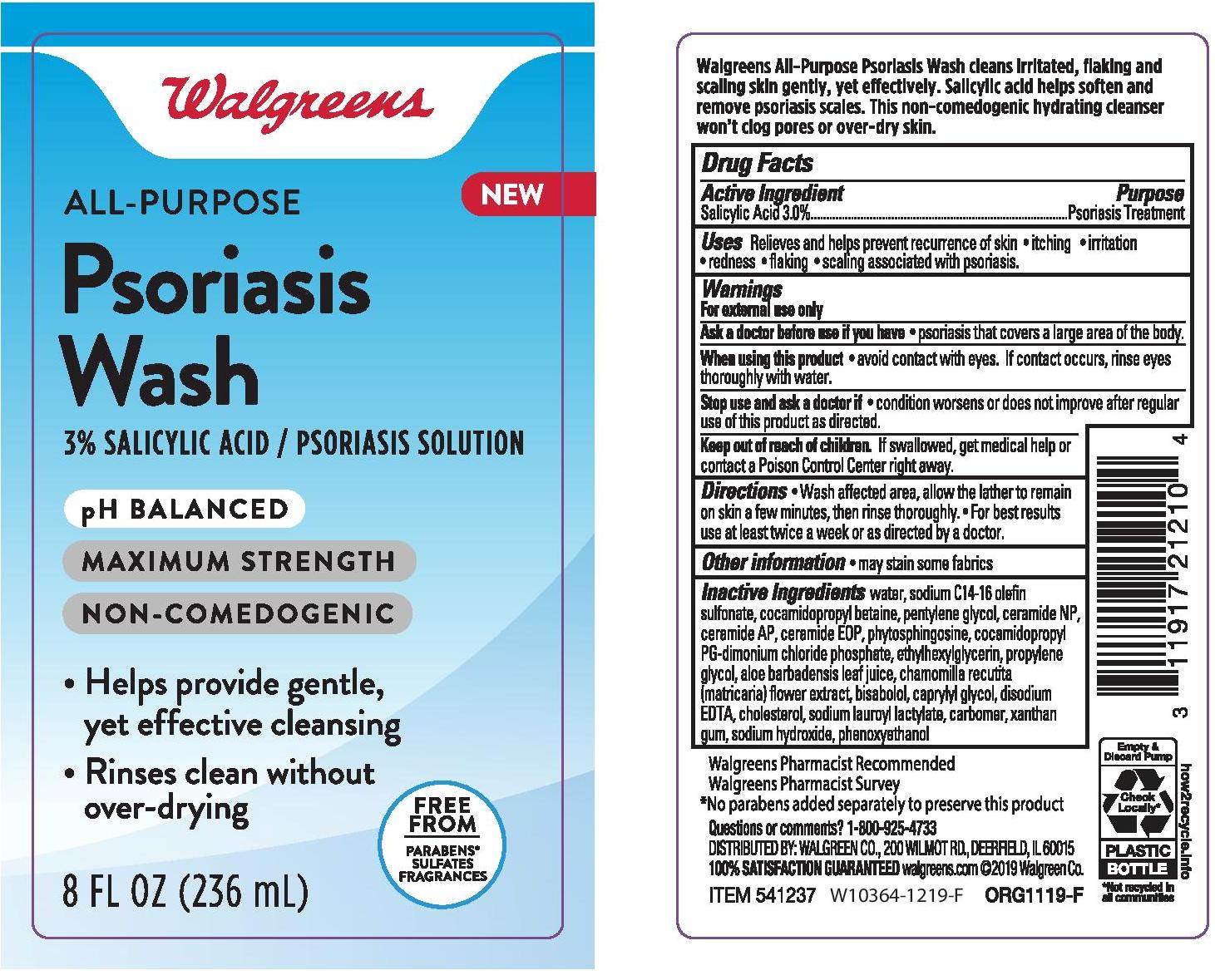 DRUG LABEL: WALGREENS ALL PURPOSE PSORIASIS WASH
NDC: 0363-0905 | Form: LIQUID
Manufacturer: WALGREEN COMPANY
Category: otc | Type: HUMAN OTC DRUG LABEL
Date: 20241014

ACTIVE INGREDIENTS: SALICYLIC ACID 30 mg/1 mL
INACTIVE INGREDIENTS: CAPRYLYL GLYCOL; CERAMIDE NP; CERAMIDE 1; SODIUM HYDROXIDE; PHYTOSPHINGOSINE; PROPYLENE GLYCOL; CHOLESTEROL; CARBOMER HOMOPOLYMER TYPE B (ALLYL SUCROSE CROSSLINKED); EDETATE DISODIUM; GLYCERIN; COCAMIDOPROPYL BETAINE; CHAMOMILE; SODIUM LAUROYL LACTYLATE; SODIUM CHLORIDE; LEVOMENOL; SODIUM C14-16 OLEFIN SULFONATE; COCAMIDOPROPYL PG-DIMONIUM CHLORIDE PHOSPHATE; PENTYLENE GLYCOL; ALOE VERA LEAF; ETHYLHEXYLGLYCERIN; PHENOXYETHANOL; XANTHAN GUM; WATER; CERAMIDE AP

WALGREENS ALL-PURPOSE PSORIASIS WASH

Active Ingredient

Salicylic Acid 3.0%

Purpose

Psoriasis Treatment

INDICATIONS AND USAGE

Uses Relieves and helps prevent recurrence of skin

- itching
- irritation
- redness
- flaking
- scaling associates with psoriasis.

Warnings

For external use only

Ask a doctor before use if you have

- psoriasis that covers a large area of the body.

When using this produt

- avoid contact with eyes. If contact occurs, rinse eyes thoroughly with water.

Stop use and ask a doctor if

- condition worsens or does not improve after regular use of this product as directed.

Keep out of reach of children.

If swallowed, get medical help or contact a Poison Control Center right away.

Directions

- Wash affected area, allow the lather to remain on skin a few minutes, then rinse thoroughly.
- For best results use at least twice a week or as directed by a doctor.

Other information

- may stain some fabrics

Inactive Ingredients

water, sodium C14-16 olefin sulfonate, cocamidopropyl betain, pentylene glycol, ceramide NP, ceramide AP, ceramide EOP, phyotsphingosine, cocamidopropyl PG-dimonium chloride phosphate, ethylhexylglycerin, propylene glycol, aloe barbadensis leaf juice, chamomilla recutita (matricaraia) flower extract, bisabolol, caprylyl glycol, disodium EDTA, cholesterol, sodium lauroyl lactylate, carbomer, xanthan gum, sodium hydroxide, phenoxyethanol

Questions or comments? 1-800-925-4733

PACKAGE LABEL

WALGREENS ALL-PURPOSE PSORIASIS WASH

8 FL OZ. (236mL)

NDC 0363-0905-11